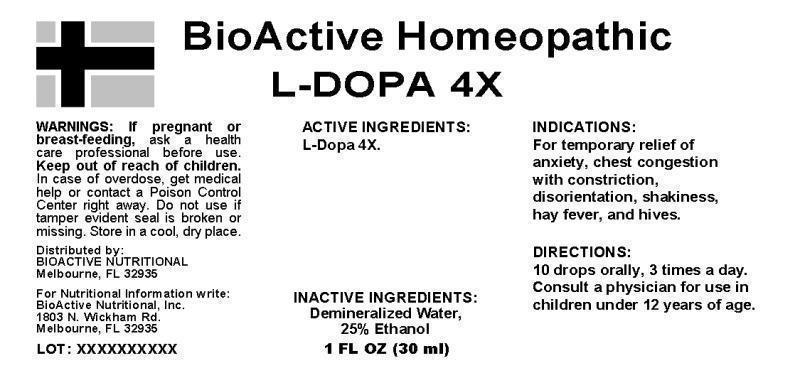 DRUG LABEL: L DOPA
NDC: 43857-0265 | Form: LIQUID
Manufacturer: BioActive Nutritional, Inc.
Category: homeopathic | Type: HUMAN OTC DRUG LABEL
Date: 20241017

ACTIVE INGREDIENTS: LEVODOPA 4 [hp_X]/1 mL
INACTIVE INGREDIENTS: WATER; ALCOHOL

DRUG FACTS:

ACTIVE INGREDIENTS:

L-dopa 4X

INDICATIONS:

For temporary relief of anxiety, chest congestion with constriction, disorientation, shakiness, hay fever, and hives

WARNINGS:

If pregnant or breast-feeding, ask a health care professional before use.

Keep out of reach of children. In case of overdose, get medical help or contact a Poison Control Center right away.

Do not use if tamper evident seal is broken or missing.

Store in cool, dry place.

Keep out of reach of children. In case of overdose, get medical help or contact a Poison Control Center right away.

DIRECTIONS:

10 drops orally, 3 times a day. Consult a physician for use in children under 12 years of age.

INDICATIONS:

For temporary relief of anxiety, chest congestion with constriction, disorientation, shakiness, hay fever, and hives

INACTIVE INGREDIENTS:

Demineralized water, 25% Ethanol.

QUESTIONS:

Distributed by:

BIOACTIVE NUTRITIONAL

Melbourne, FL 32935

For Nutritional Information write:

BioActive Nutritional, Inc.

1803 N. Wickham Rd.

Melbourne, FL 32935

PACKAGE LABEL DISPLAY:

BioActive Homeopathic

L-DOPA 4X

1 FL OZ (30 ml)